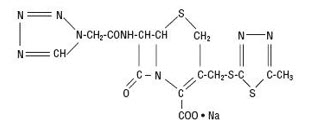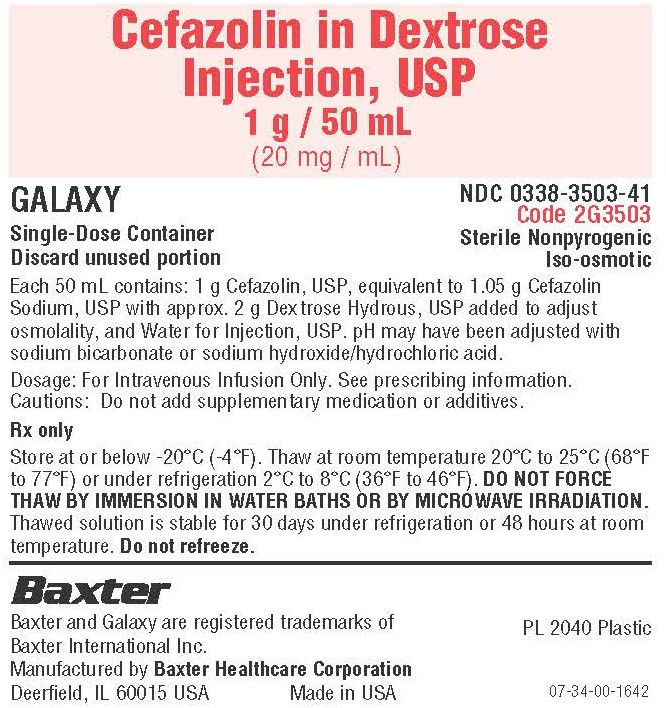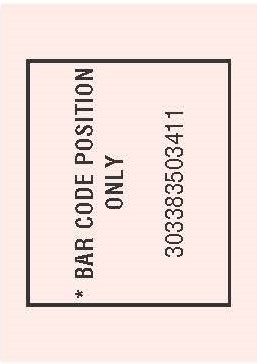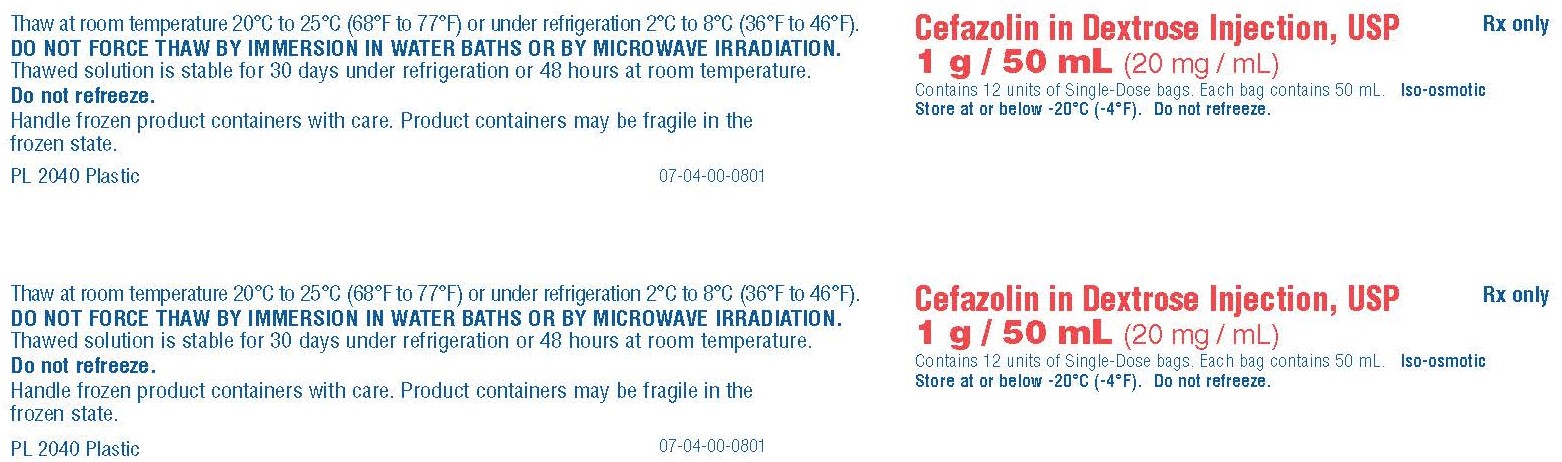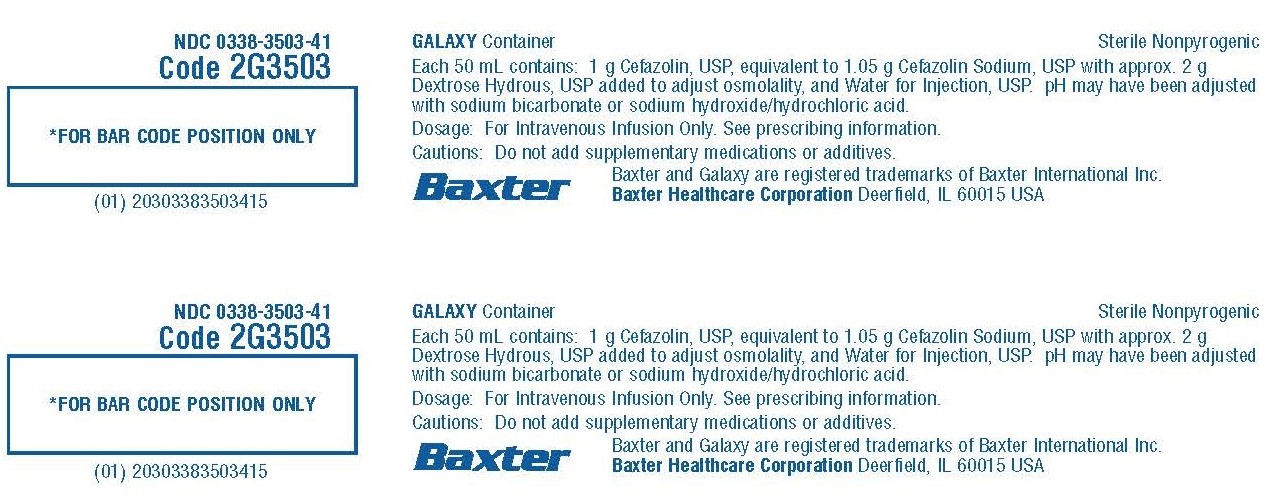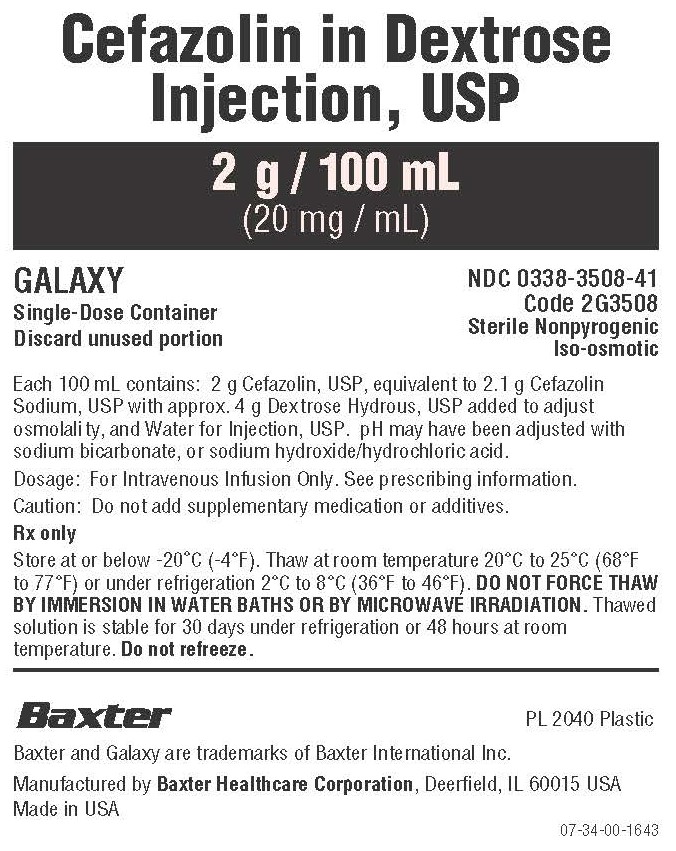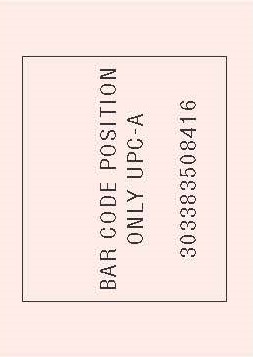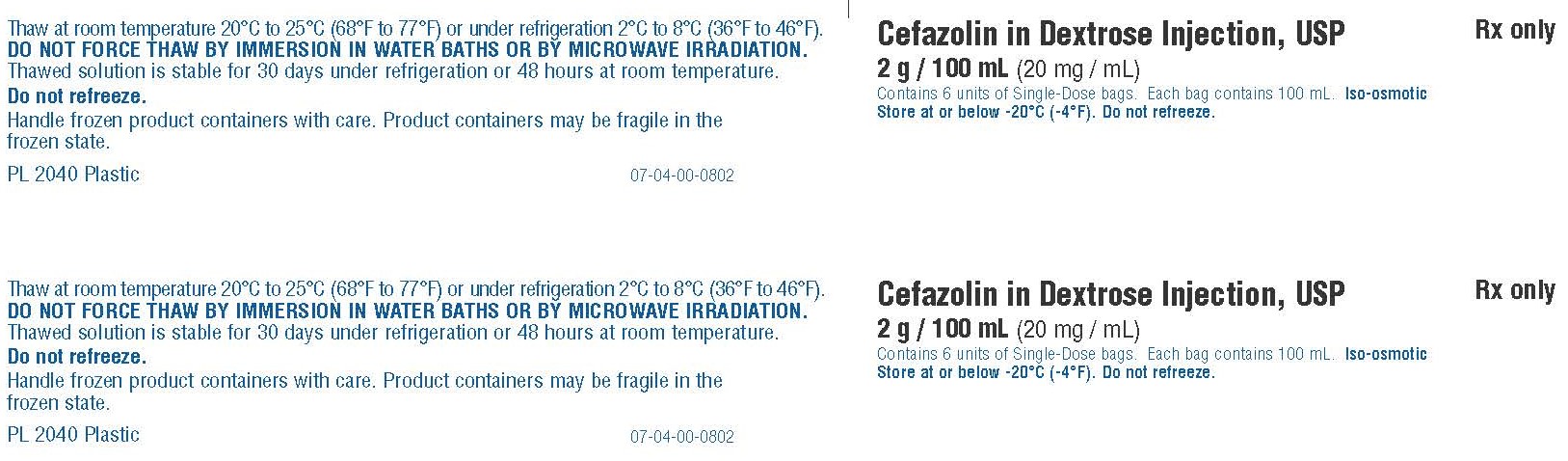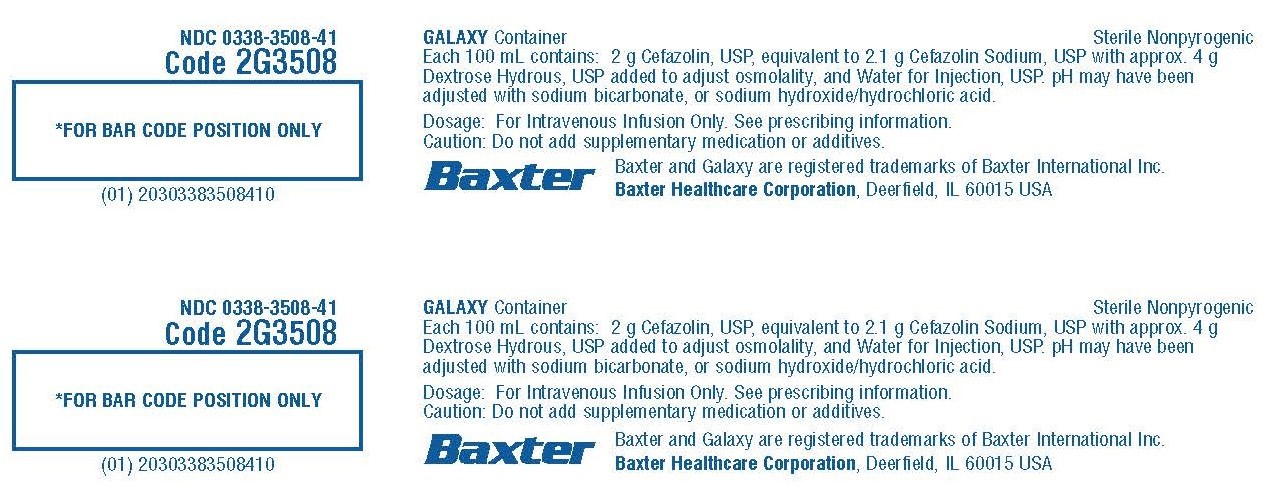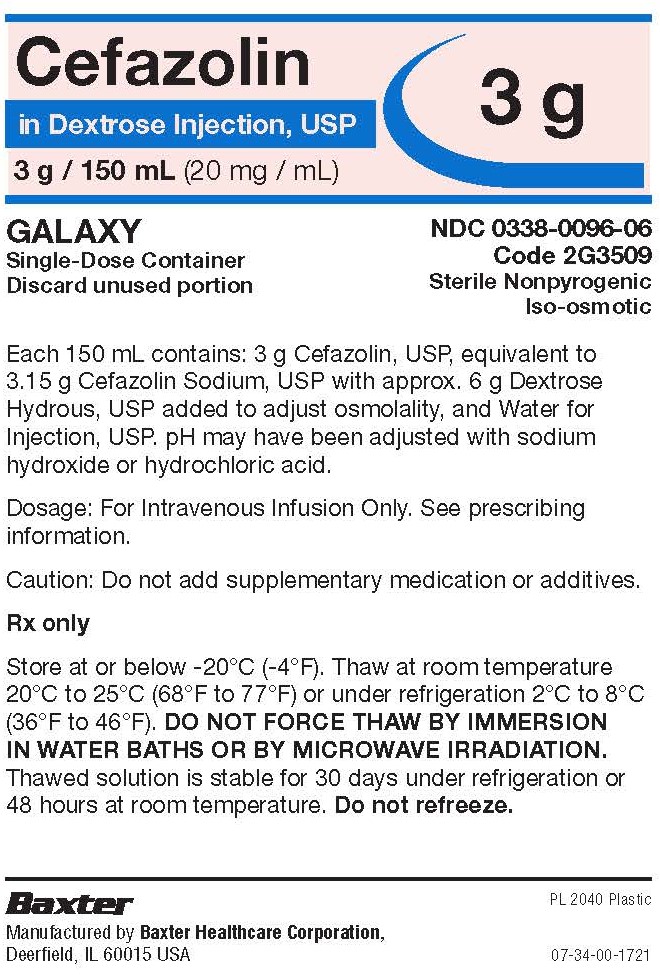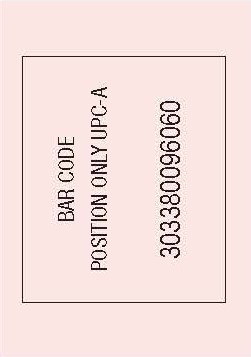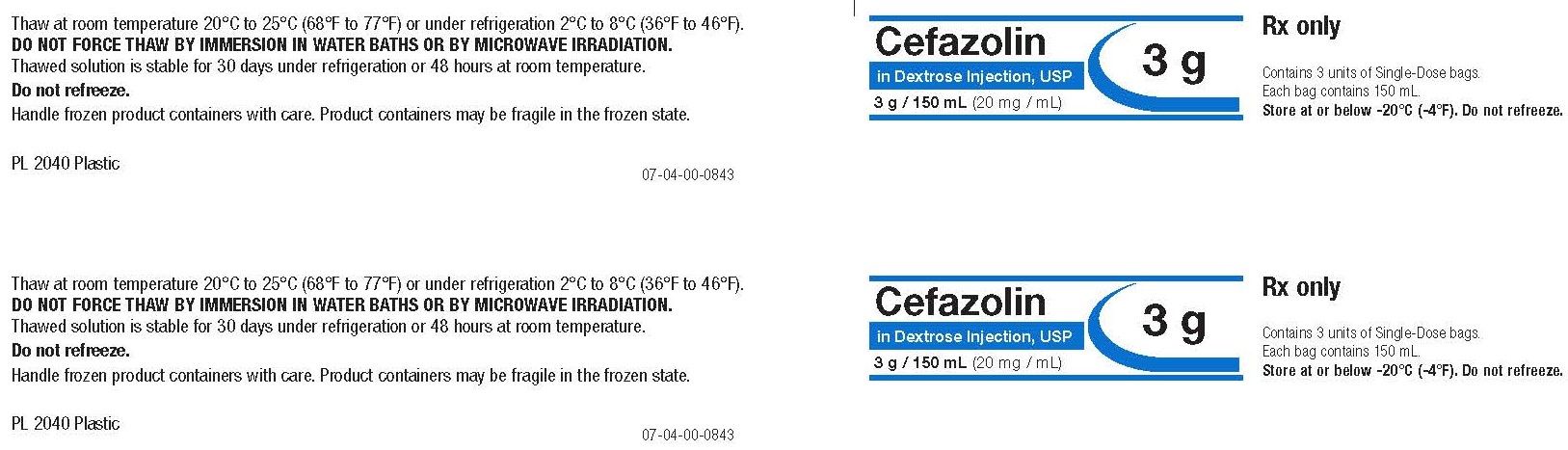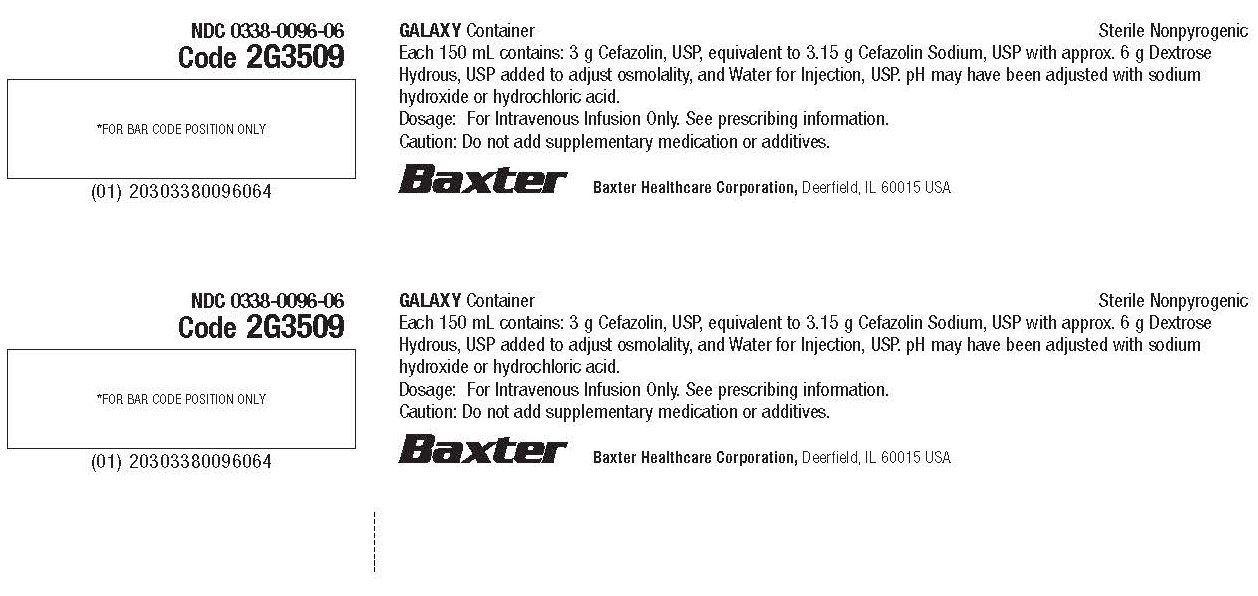 DRUG LABEL: Cefazolin
NDC: 0338-3508 | Form: INJECTION, SOLUTION
Manufacturer: Baxter Healthcare Corporation
Category: prescription | Type: HUMAN PRESCRIPTION DRUG LABEL
Date: 20251210

ACTIVE INGREDIENTS: CEFAZOLIN SODIUM 2 g/100 mL
INACTIVE INGREDIENTS: ANHYDROUS DEXTROSE 4 g/100 mL; SODIUM BICARBONATE; WATER; HYDROCHLORIC ACID; SODIUM HYDROXIDE

HIGHLIGHTS OF PRESCRIBING INFORMATION

These highlights do not include all the information needed to use CEFAZOLIN IN DEXTROSE INJECTION safely and effectively. See full prescribing information for CEFAZOLIN IN DEXTROSE INJECTION.
CEFAZOLIN IN DEXTROSE injection, for intravenous use
Initial U.S. Approval: 1973

RECENT MAJOR CHANGES

Warnings and Precautions, Hypersensitivity Reactions to Cefazolin, Cephalosporins, Penicillins, or Other Beta-lactams (5.1) 12/2025

1 INDICATIONS AND USAGE

Cefazolin in Dextrose Injection is a cephalosporin antibacterial indicated for:

- Treatment of the following infections caused by susceptible isolates of the designated microorganisms in adult and pediatric patients for whom appropriate dosing with this formulation can be achieved: (1)
  ο Respiratory tract infections (1.1);
  ο Urinary tract infections (1.2);
  ο Skin and skin structure infections (1.3);
  ο Biliary tract infections (1.4);
  ο Bone and joint infections (1.5);
  ο Genital infections (1.6);
  ο Septicemia (1.7);
  ο Endocarditis (1.8)
- Perioperative prophylaxis in adults and pediatric patients aged 10 to 17 years old for whom appropriate dosing with this formulation can be achieved (1.9)

To reduce the development of drug-resistant bacteria and maintain the effectiveness of Cefazolin in Dextrose Injection and other antibacterial drugs, Cefazolin in Dextrose Injection should be used only to treat or prevent infections that are proven or strongly suspected to be caused by bacteria. (1.10).

2 DOSAGE AND ADMINISTRATION

If a dose of Cefazolin in Dextrose Injection is required that does not equal 1 gram, 2 grams or 3 grams, this product is not recommended for use and an alternative formulation of cefazolin should be considered. (2.1)
For intravenous use only administered over approximately 30 minutes. (2.1)

Recommended Dosing Schedule in Adult Patients with CLcr Greater Than or Equal To 55 m L/min. (2.1)
Site and Type of Infection | Dose | Frequency
Moderate to severe infections | 500 mg to 1 gram | every 6 to 8 hours
Mild infections caused by susceptible gram-positive cocci | 250 mg to 500 mg | every 8 hours
Acute, uncomplicated urinary tract infections | 1 gram | every 12 hours
Pneumococcal pneumonia | 500 mg | every 12 hours
Severe, life-threatening infections (e.g., endocarditis, septicemia) [In rare instances, doses of up to 12 grams of cefazolin per day have been used] | 1 gram to 1.5 grams | every 6 hours
Perioperative prophylaxis | less than 120 kg: 1 gram to 2 grams | ½ to 1 hour prior to start of surgery
Perioperative prophylaxis | greater than or equal to 120 kg: 3 grams | ½ to 1 hour prior to start of surgery
Perioperative prophylaxis | 500 mg to 1 gram | additional dose during surgery for lengthy procedures
Perioperative prophylaxis | 500 mg to 1 gram | every 6 to 8 hours for 24 hours postoperatively

Recommended Dosing Schedule in Pediatric Patients with CLcr Greater than or Equal to 70 mL/min. (2.1, 2.2, and 2.3)
Site and Type of Infection | Dose | Frequency
Moderate to severe infections [For the treatment indications (1.1 to 1.8)] | 25 to 50 mg per kg | divided into 3 or 4 equal doses
Severe infections | May increase to 100 mg per kg | divided into 3 or 4 equal doses
Perioperative prophylaxis (10 to 17 years old) | less than 50 kg: 1 gram | ½ to 1 hour prior to start of surgery
Perioperative prophylaxis (10 to 17 years old) | greater than or equal to 50 kg: 2 grams | ½ to 1 hour prior to start of surgery
Perioperative prophylaxis (10 to 17 years old) | 500 mg to 1 g | additional dose during surgery for lengthy procedures
Perioperative prophylaxis (10 to 17 years old) | 500 mg to 1 g | every 6 to 8 hours for 24 hours postoperatively

- Dosage adjustment is required for adult patients with CLcr that is less than 55 mL/min and pediatric patients with CLcr that is less than 70 mL/min. (2.4 and 8.6)
- See full prescribing information for preparation and administration instructions. (2.5)

3 DOSAGE FORMS AND STRENGTHS

Injection: 1 gram in 50 mL, 2 grams in 100 mL and 3 grams in 150 mL (3)

4 CONTRAINDICATIONS

Hypersensitivity to cefazolin or other cephalosporin class antibacterial drugs, penicillins, or other beta-lactams (4.1)

5 WARNINGS AND PRECAUTIONS

- Hypersensitivity Reactions: Cross-hypersensitivity may occur in up to 10% of patients with a history of penicillin allergy. If an allergic reaction occurs, discontinue the drug. (5.1)
- Clostridioides difficile-associated Diarrhea (CDAD): May range from mild diarrhea to fatal colitis. Evaluate if diarrhea occurs. (5.3)
- Prothrombin Activity: May be associated with a fall in prothrombin activity. Prothrombin time should be monitored in patients at risk and exogenous vitamin K administered as indicated (5.5)

6 ADVERSE REACTIONS

- Adult and Pediatric Patients: Most common adverse reactions: gastrointestinal (nausea, vomiting, diarrhea), and allergic reactions (anaphylaxis, urticaria, skin rash). (6)
- Pediatric Patients with Perioperative Prophylaxis: The most frequently reported adverse reactions (incidence ≥ 5%) were nausea, infusion site pain, and headache. (6)

To report SUSPECTED ADVERSE REACTIONS, contact Baxter Healthcare at 1-866-888-2472 or FDA at 1-800-FDA-1088 or www.fda.gov/medwatch.

7 DRUG INTERACTIONS

Probenecid: The renal excretion of cefazolin is inhibited by probenecid. Co-administration of probenecid with Cefazolin in Dextrose Injection is not recommended. (7)

FULL PRESCRIBING INFORMATION

1 INDICATIONS AND USAGE

1.1 Respiratory Tract Infections

Cefazolin in Dextrose Injection is indicated for the treatment of respiratory tract infections due to Streptococcus pneumoniae, Staphylococcus aureus and Streptococcus pyogenes in adults and pediatric patients for whom appropriate dosing with this formulation can be achieved [see Dosage and Administration (2.1, 2.2, 2.4 and 2.5) and Use in Specific Populations (8.4)].

Limitations of Use

Injectable benzathine penicillin is considered the drug of choice in treatment and prevention of streptococcal infections, including the prophylaxis of rheumatic fever.

Cefazolin in Dextrose Injection is effective in the eradication of streptococci from the nasopharynx; however, data establishing the efficacy of cefazolin in the subsequent prevention of rheumatic fever are not available.

1.2 Urinary Tract Infections

Cefazolin in Dextrose Injection is indicated for the treatment of urinary tract infections due to Escherichia coli, and Proteus mirabilis in adults and pediatric patients for whom appropriate dosing with this formulation can be achieved [see Dosage and Administration (2.1, 2.2, 2.4 and 2.5) and Use in Specific Populations (8.4)].

1.3 Skin and Skin Structure Infections

Cefazolin in Dextrose Injection is indicated for the treatment of skin and skin structure infections due to S. aureus, S. pyogenes, and Streptococcus agalactiae in adults and pediatric patients for whom appropriate dosing with this formulation can be achieved [see Dosage and Administration (2.1, 2.2, 2.4 and 2.5) and Use in Specific Populations (8.4)].

1.4 Biliary Tract Infections

Cefazolin in Dextrose Injection is indicated for the treatment of biliary infections due to E. coli, various isolates of streptococci, P. mirabilis, and S. aureus in adults and pediatric patients for whom appropriate dosing with this formulation can be achieved [see Dosage and Administration (2.1, 2.2, 2.4 and 2.5) and Use in Specific Populations (8.4)].

1.5 Bone and Joint Infections

Cefazolin in Dextrose Injection is indicated for the treatment of bone and joint infections due to S. aureus in adults and pediatric patients for whom appropriate dosing with this formulation can be achieved [see Dosage and Administration (2.1, 2.2, 2.4 and 2.5) and Use in Specific Populations (8.4)].

1.6 Genital Infections

Cefazolin in Dextrose Injection is indicated for the treatment of genital infections due to E. coli, and P. mirabilis in adults and pediatric patients for whom appropriate dosing with this formulation can be achieved [see Dosage and Administration (2.1, 2.2, 2.4 and 2.5) and Use in Specific Populations (8.4)].

1.7 Septicemia

Cefazolin in Dextrose Injection is indicated for the treatment of septicemia due to S. pneumoniae, S. aureus, P. mirabilis, and E. coli in adults and pediatric patients for whom appropriate dosing with this formulation can be achieved [see Dosage and Administration (2.1, 2.2, 2.4 and 2.5) and Use in Specific Populations (8.4)].

1.8 Endocarditis

Cefazolin in Dextrose Injection is indicated for the treatment of endocarditis due to S. aureus and S. pyogenes in adults and pediatric patients for whom appropriate dosing with this formulation can be achieved [see Dosage and Administration (2.1, 2.2, 2.4 and 2.5) and Use in Specific Populations (8.4)].

1.9 Perioperative Prophylaxis

Cefazolin in Dextrose Injection is indicated for perioperative prophylaxis in adults and pediatric patients aged 10 to 17 years old for whom appropriate dosing with this formulation can be achieved [see Dosage and Administration (2.1, 2.3, 2.4, 2.5) and Use in Specific Populations (8.4)].

The perioperative use of Cefazolin in Dextrose Injection is indicated in adult and pediatric (aged 10 to 17 years old) surgical patients in whom infection at the operative site would present a serious risk (e.g., during open-heart surgery and prosthetic arthroplasty).

The prophylactic administration of Cefazolin in Dextrose Injection preoperatively, intraoperatively, and postoperatively may reduce the incidence of certain postoperative infections in patients undergoing surgical procedures which are classified as contaminated or potentially contaminated (e.g., vaginal hysterectomy, and cholecystectomy in high-risk patients such as those older than 70 years, with acute cholecystitis, obstructive jaundice, or common duct bile stones).

1.10 Usage

To reduce the development of drug-resistant bacteria and maintain the effectiveness of Cefazolin in Dextrose Injection and other antibacterial drugs, Cefazolin in Dextrose Injection should be used only to treat or prevent infections that are proven or strongly suspected to be caused by susceptible bacteria. When culture and susceptibility information are available, they should be considered in selecting or modifying antibacterial therapy. In the absence of such data, local epidemiology and susceptibility patterns may contribute to the empiric selection of therapy.

2 DOSAGE AND ADMINISTRATION

2.1 Important Administration Instructions

If a dose of Cefazolin in Dextrose Injection is required that does not equal 1 gram, 2 grams or 3 grams, this product is not recommended for use and an alternative formulation of cefazolin should be considered.

Administer Cefazolin in Dextrose Injection intravenously over approximately 30 minutes.

2.2 Dosage for the Treatment of Infections

Dosage for the Treatment of Infections in Adults with Creatinine Clearance (CLcr) Equal to 55 mL/min or Greater

The recommended adult dosages for the treatment of infections [see Indications and Usage (1.1 to 1.8)] are outlined in Table 1 below. Administer Cefazolin in Dextrose Injection intravenously over approximately 30 minutes.

Table 1: Recommended Dosing Schedule in Adult Patients with CLcr Greater Than or Equal To 55 mL/min. [If a dose of Cefazolin in Dextrose Injection is required that does not equal 1 gram, 2 grams, or 3 grams, this product is not recommended for use and an alternative formulation of cefazolin should be considered.]
Site and Type of Infection | Dose | Frequency
Moderate to severe infections | 500 mg to 1 gram | every 6 to 8 hours
Mild infections caused by susceptible gram-positive cocci | 250 mg to 500 mg | every 8 hours
Acute, uncomplicated urinary tract infections | 1 gram | every 12 hours
Pneumococcal pneumonia | 500 mg | every 12 hours
Severe, life-threatening infections (e.g., endocarditis, septicemia) [In rare instances, doses of up to 12 grams of cefazolin per day have been used.] | 1 gram to 1.5 grams | every 6 hours

Dosage for the Treatment of Infections in Pediatric Patients with CLcr Equal to 70 mL/min or Greater

The recommended pediatric dosages for the treatment of infections [see Indications and Usage (1.1 to 1.8)] are outlined in Table 2 below. Administer Cefazolin in Dextrose Injection intravenously over approximately 30 minutes.

If a dose of Cefazolin in Dextrose Injection is required that does not equal 1 gram, 2 grams, or 3 grams, this product is not recommended for use and an alternative formulation of cefazolin should be considered [see Use in Specific Populations (8.4)].

Table 2: Recommended Dosage in Pediatric Patients with CLcr 70 mL/min or greater for Treatment of Infections [see Indications and Usage (1.1 to 1.8)]
Type of Severity | Recommended Total Daily Dosage
Mild to moderate infections | 25 mg/kg to 50 mg/kg, divided into 3 or 4 equal doses
Severe infections | May increase to 100 mg/kg, divided into 3 or 4 equal doses

2.3 Dosage for Perioperative Prophylaxis

Dosage for Perioperative Prophylaxis in Adults with CLcr Equal to 55 mL/min or Greater

To prevent postoperative infection in contaminated or potentially contaminated surgery, recommended dosages are described in Table 3 below.

Table 3: Recommended Dosage for Perioperative Prophylaxis in Adults with CLcr of 55 mL/min or Greater
Body Weight (kg) | Dose Administered (½ hour to 1 hour prior to the start of surgery) | Additional Dose During Lengthy Operative Procedures (e.g., 2 hours or more) | Dose for 24 Hours Postoperatively
Less than 120 kg | 1 gram to 2 grams | 500 mg to 1 g | 500 mg to 1 g every 6 hours to 8 hours
Greater than or equal to 120 kg | 3 grams | 500 mg to 1 g | 500 mg to 1 g every 6 hours to 8 hours

If a dose of Cefazolin in Dextrose Injection is required that does not equal 1 gram, 2 grams, or 3 grams, this product is not recommended, and an alternative formulation of cefazolin should be considered.

It is important that (i) the preoperative dose be given just prior (1/2 hour to 1 hour) to the start of surgery so that adequate antibacterial concentrations are present in the serum and tissues at the time of initial surgical incision; and (ii) cefazolin be administered, if necessary, at appropriate intervals during surgery to provide sufficient concentrations of the antibacterial drug at the anticipated moments of greatest exposure to infective organisms.

The perioperative prophylactic administration of cefazolin should usually be discontinued within a 24-hour period after the surgical procedure. In surgery where the occurrence of infection may be particularly devastating (e.g., open-heart surgery and prosthetic arthroplasty), the prophylactic administration of cefazolin may be continued for 3 to 5 days following the completion of surgery.

Dosage for Perioperative Prophylaxis in Pediatric Patients Aged 10 to 17 Years Old with CLcr 70 mL/min or Greater

To prevent postoperative infection in contaminated or potentially contaminated surgery, recommended doses are described in Table 4 below.

Table 4: Recommended Dosage for Perioperative Prophylaxis in Pediatric with CLcr 70 mL/min or greater Aged 10 to 17 years Old [If a dose of Cefazolin in Dextrose Injection is required that does not equal 1 gram or 2 grams, this product is not recommended for use and an alternative formulation of cefazolin should be considered.]
Body Weight (kg) | Dose Administered ½ Hour to 1 Hour Prior to the Start of Surgery | Additional Dose During Lengthy Operative Procedures (e.g., 2 Hours or More) | Dose for 24 Hours Postoperatively
Less than 50 kg | 1 g | 500 mg to 1 g | 500 mg to 1 g every 6 hours to 8 hours
Greater than or equal to 50 kg | 2 g | 500 mg to 1 g | 500 mg to 1 g every 6 hours to 8 hours

It is important that (i) the preoperative dose be given just prior (1/2 hour to 1 hour) to the start of surgery so that adequate antibacterial concentrations are present in the serum and tissues at the time of initial surgical incision; and (ii) cefazolin be administered, if necessary, at appropriate intervals during surgery to provide sufficient concentrations of the antibacterial drug at the anticipated moments of greatest exposure to infective organisms.

The administration of Cefazolin in Dextrose Injection for perioperative prophylaxis should usually be discontinued within a 24-hour period after the surgical procedure. In surgery where the occurrence of infection may be particularly devastating the administration of Cefazolin in Dextrose Injection for perioperative prophylaxis may be continued for 3 days to 5 days following the completion of surgery.

2.4 Dosage Recommendations in Adult and Pediatric Patients with Renal Impairment

Dosage Recommendations in Adult Patients with CLcr less than 55 mL/min

The dosage recommendation for Cefazolin in Dextrose Injection in adult patients with renal impairment (CLcr less than 55 mL/min) is outlined in Table 5 below.

Table 5: Dosage Recommendation for Adult Patients with CLcr less than 55 mL/min
Creatinine Clearance | Dose | Frequency
35 to 54 mL/min | Recommended dose | every 8 hours or longer
11 to 34 mL/min | Half of recommended dose [If the recommended dose in adult patients with creatinine clearance equal to 35 mL/min or greater is 1 gram, then this product is not recommended for use in patients with creatinine clearance less than 35 mL/min and an alternative formulation of cefazolin should be considered.] | every 12 hours
10 mL/min or less | Half of recommended dose | every 18 to 24 hours

Dosage Recommendations in Pediatric Patients with CLcr less than 70 mL/min

The dosage recommendation for Cefazolin in Dextrose Injection in pediatric patients with renal impairment (CLcr less than 70 mL/min) is outlined in Table 6 below.

Table 6: Recommended Dosage in Pediatric Patients with CLcr less than 70 mL/min [If a dose of Cefazolin in Dextrose Injection is required that does not equal 1 gram, 2 or 3 grams, this product is not recommended for use and an alternative formulation of cefazolin should be considered.]
Creatinine Clearance | Recommended Dosage
40 to 70 mL/min | 60% of the normal daily dose given in equally divided doses every 12 hours
20 to 40 mL/min | 25% of the normal daily dose given in equally divided doses every 12 hours
5 to 20 mL/min | 10% of the normal daily dose every 24 hours

2.5 Preparation for Use of Cefazolin in Dextrose Injection

Thawing of Plastic Container

- Thaw frozen container at room temperature 20°C to 25°C (68°F to 77°F) or under refrigeration 2°C to 8°C (36°F to 46°F). Product should not be thawed by immersion in water baths or by microwave irradiation. Do not force thaw.
- No further dilution is necessary.
- Check for minute leaks by squeezing container firmly. If leaks are detected, discard solution as sterility may be impaired.
- Do not add supplementary medication.
- The container should be visually inspected. If the outlet port protector is damaged, detached, or not present, discard container as solution path sterility may be impaired. Components of the solution may precipitate in the frozen state and will dissolve upon reaching room temperature with little or no agitation. Potency is not affected. Agitate after solution has reached room temperature. If after visual inspection the solution remains cloudy or if an insoluble precipitate is noted or if any seals are not intact, the container should be discarded.
- The thawed solution is stable for 30 days under refrigeration (5°C/41°F) or 48 hours at 25°C/77°F. Do not refreeze thawed antibacterial drugs.

Preparation for Administration

- Suspend container from support.
- Remove protector from outlet port at bottom of container.
- Attach Intravenous administration set to outlet port. Refer to the manufacturer’s instructions accompanying the administration set for complete directions.

3 DOSAGE FORMS AND STRENGTHS

Injection: 1 gram cefazolin per 50 mL, 2 gram cefazolin per 100 mL or 3 gram cefazolin per 150 mL in a single-dose Galaxy container supplied as a frozen, premixed, iso-osmotic, sterile, nonpyrogenic solution.

4 CONTRAINDICATIONS

4.1 Hypersensitivity to Cefazolin or the Cephalosporin Class of Antibacterial Drugs, Penicillins, or Other Beta-lactams

Cefazolin in Dextrose Injection is contraindicated in patients who have a history of immediate hypersensitivity reactions (e.g., anaphylaxis, serious skin reactions) to cefazolin or the cephalosporin class of antibacterial drugs, penicillins, or other beta-lactams [see Warnings and Precautions (5.1)].

5 WARNINGS AND PRECAUTIONS

5.1 Hypersensitivity Reactions to Cefazolin, Cephalosporins, Penicillins, or Other Beta-lactams

Serious and occasionally fatal hypersensitivity (anaphylactic) reactions have been reported in patients receiving beta-lactam antibacterial drugs. Hypersensitivity reactions can progress to Kounis syndrome, a serious allergic reaction that can result in myocardial infarction. Before therapy with Cefazolin in Dextrose Injection is instituted, careful inquiry should be made to determine whether the patient has had previous immediate hypersensitivity reactions to cefazolin, cephalosporins, penicillins, or carbapenems. Exercise caution if this product is to be given to penicillin-sensitive patients because cross-hypersensitivity among beta-lactam antibacterial drugs has been clearly documented and may occur in up to 10% of patients with a history of penicillin allergy. If an allergic reaction to Cefazolin in Dextrose Injection occurs, discontinue the drug.

5.2 Seizures in Patients with Renal Impairment

Seizures may occur with the administration of Cefazolin in Dextrose Injection, particularly in patients with renal impairment when the dosage is not reduced appropriately. Discontinue Cefazolin in Dextrose Injection if seizures occur or make appropriate dosage adjustments in patients with renal impairment [see Dosage and Administration (2.4)]. Anticonvulsant therapy should be continued in patients with known seizure disorders.

5.3 Clostridioides difficile-associated Diarrhea

Clostridioides difficile-associated diarrhea (CDAD) has been reported with use of nearly all antibacterial agents, including cefazolin, and may range in severity from mild diarrhea to fatal colitis. Treatment with antibacterial agents alters the normal flora of the colon leading to overgrowth of C. difficile.

C. difficile produces toxins A and B, which contribute to the development of CDAD. Hypertoxin-producing isolates of C. difficile cause increased morbidity and mortality, as these infections can be refractory to antimicrobial therapy and may require colectomy. CDAD must be considered in all patients who present with diarrhea following antibacterial drug use. Careful medical history is necessary since CDAD has been reported to occur over two months after the administration of antibacterial agents.

If CDAD is suspected or confirmed, ongoing antibacterial drug use not directed against C. difficile may need to be discontinued. Appropriate fluid and electrolyte management, protein supplementation, antibacterial drug treatment of C. difficile, and surgical evaluation should be instituted as clinically indicated.

5.4 Hypersensitivity to Dextrose-containing Products

Hypersensitivity reactions, including anaphylaxis, have been reported with administration of dextrose- containing products. These reactions have been reported in patients receiving high concentrations of dextrose (i.e. 50% dextrose)^1. The reactions have also been reported when corn-derived dextrose solutions were administered to patients with or without a history of hypersensitivity to corn products.^2

5.5 Prothrombin Activity

Cefazolin in Dextrose Injection may be associated with a fall in prothrombin activity. Those at risk include patients with renal or hepatic impairment or poor nutritional state, as well as patients receiving a protracted course of antimicrobial therapy, and patients previously stabilized on anticoagulant therapy. Prothrombin time should be monitored in patients at risk and exogenous vitamin K administered as indicated.

5.6 Risk of Development of Drug-resistant Bacteria

Prescribing Cefazolin in Dextrose Injection in the absence of proven or strongly suspected bacterial infection or a prophylactic indication is unlikely to provide benefit to the patient and increases the risk of the development of drug-resistant bacteria.

As with other antimicrobials, prolonged use of Cefazolin in Dextrose Injection may result in overgrowth of nonsusceptible microorganisms. Repeated evaluation of the patient's condition is essential. Should superinfection occur during therapy, appropriate measures should be taken.

5.7 Drug/Laboratory Test Interactions

Urinary Glucose

The administration of Cefazolin in Dextrose Injection may result in a false-positive reaction with glucose in the urine when using glucose tests based on Benedict’s copper reduction reaction that determine the amount of reducing substances like glucose in the urine. It is recommended that glucose tests based on enzymatic glucose oxidase be used.

Coombs’ Test

Positive direct Coombs' tests have been reported during treatment with cefazolin. In hematologic studies or in transfusion cross-matching procedures when antiglobulin tests are performed on the minor side or in Coombs' testing of newborns whose mothers have received cephalosporin antibacterial drugs before parturition, it should be recognized that a positive Coombs' test may be due to the drug.

5.8 Patients with Overt or Known Subclinical Diabetes Mellitus or Carbohydrate Intolerance

As with other dextrose-containing solutions, Cefazolin in Dextrose Injection should be prescribed with caution in patients with overt or known subclinical diabetes mellitus or carbohydrate intolerance for any reason.

6 ADVERSE REACTIONS

The following serious adverse reactions to Cefazolin in Dextrose Injection are described below and elsewhere in the labeling:

- Hypersensitivity Reactions to Cefazolin, Cephalosporins, Penicillins, or Other Beta-lactams [see Warnings and Precautions (5.1)]
- Seizures in Patients with Renal Impairment [see Warnings and Precautions (5.2)]
- Clostridioides difficile-associated Diarrhea [see Warnings and Precautions (5.3)]

6.1 Clinical Trials Experience

Because clinical trials are conducted under widely varying conditions, adverse reaction rates observed in the clinical trials of a drug cannot be directly compared to rates in the clinical trials of another drug and may not reflect the rates observed in practice.

The following adverse reactions were reported from clinical trials:

Gastrointestinal: Diarrhea, oral candidiasis (oral thrush), mouth ulcers, vomiting, nausea, stomach cramps, epigastric pain, heartburn, flatus, anorexia and pseudomembranous colitis. Onset of pseudomembranous colitis symptoms may occur during or after antibacterial treatment [see Warnings and Precautions (5.3)].

Allergic: Anaphylaxis, eosinophilia, urticaria, itching, drug fever, skin rash, Stevens-Johnson syndrome.

Hematologic: Neutropenia, leukopenia, thrombocytopenia, thrombocythemia.

Hepatic: Transient rise in SGOT, SGPT, and alkaline phosphatase levels has been observed. Reports of hepatitis have been received.

Renal: Reports of increased BUN and creatinine levels, as well as renal failure, have been received.

Local Reactions: Instances of phlebitis have been reported at site of injection. Some induration has occurred.

Other Reactions: Pruritus (including genital, vulvar and anal pruritus, genital moniliasis, and vaginitis). Dizziness, fainting, lightheadedness, confusion, weakness, tiredness, hypotension, somnolence and headache.

Adverse Reactions in Pediatric Patients for Perioperative Prophylaxis

Two studies (Study 1: NCT 3231228 and Study 2: NCT 01904357) were conducted to assess the safety and pharmacokinetics of a single 30-minute infusion of either 1 gram or 2 grams (based on weight) of cefazolin for injection and dextrose injection for perioperative prophylaxis in pediatric patients.

Study 1 was a multicenter, open-label, non-comparative, parallel group study to evaluate the safety and pharmacokinetics of a single 30-minute infusion of either 1 gram or 2 grams (based on weight) of cefazolin for injection and dextrose injection for perioperative prophylaxis in 61 pediatric patients 10 to 17 years of age. Thirty-three subjects with a weight of at least 25 kg but less than 60 kg received a single dose of 1 gram of cefazolin for injection and dextrose injection and 28 subjects with a weight of at least 60 kg received a single dose of 2 grams of cefazolin for injection and dextrose injection. The mean age of the safety population was 14 years and ranged from 10 to 17 years. There were no adverse reactions leading to study discontinuation or deaths reported during the study. The most frequently reported adverse reactions were nausea (14.8%), infusion site pain (6.6%), and headache (4.9%).

Study 2 was a multicenter, non-comparative study that evaluated the safety and pharmacokinetics of a single 30-minute infusion of either 1 gram or 2 grams (based on weight) of cefazolin for injection and dextrose injection for perioperative prophylaxis in 12 pediatric patients 10 to 12 years of age. Subjects weighing at least 25 kg to less than 50 kg received a single dose of 1 gram of cefazolin for injection and dextrose injection and subjects weighing at least 50 kg to less than 85 kg received a single dose of 2 grams of cefazolin for injection and dextrose injection. The safety findings in Study 2 in pediatric patients aged 10 to 12 years old were similar to those observed in adult patients and the pediatric patients aged 10 to 17 years old in Study 1.

6.2 Postmarketing Experience

The following adverse reactions have been identified during post approval use of cefazolin. Because these reactions are reported voluntarily from a population of uncertain size, it is not always possible to reliably estimate their frequency or establish a causal relationship to drug exposure.

Immune system disorders: Serum sickness-like reaction

Renal and urinary disorders: Acute tubulointerstitial nephritis (ATIN)

Skin and subcutaneous tissue disorders: Acute generalized exanthematous pustulosis (AGEP)

Cardiac disorders: Kounis syndrome

6.3 Cephalosporin-class Adverse Reactions

In addition to the adverse reactions listed above that have been observed in patients treated with cefazolin, the following adverse reactions and altered laboratory tests have been reported for cephalosporin-class antibacterials:

Stevens-Johnson syndrome, erythema multiforme, toxic epidermal necrolysis, renal impairment, toxic nephropathy, aplastic anemia, hemolytic anemia, hemorrhage, a fall in prothrombin activity, hepatic impairment including cholestasis, and pancytopenia.

7 DRUG INTERACTIONS

The renal excretion of cefazolin is inhibited by probenecid. Co-administration of probenecid with Cefazolin in Dextrose Injection is not recommended.

8 USE IN SPECIFIC POPULATIONS

8.1 Pregnancy

Risk Summary
Available data from published prospective cohort studies, case series and case reports over several decades with cephalosporin use, including cefazolin, in pregnant women have not established a drug-associated risk of major birth defects, miscarriage, or adverse maternal or fetal outcomes. Cefazolin crosses the placenta.

Animal reproduction studies with rats, mice and rabbits administered cefazolin during organogenesis at doses 1 to 3 times the maximum recommended human dose (MRHD) did not demonstrate adverse developmental outcomes. In rats subcutaneously administered cefazolin prior to delivery and throughout lactation, there were no adverse effects on offspring at a dose approximately 2 times the MRHD (see Data).

The estimated background risk of major birth defects and miscarriage for the indicated population is unknown. All pregnancies have a background risk of birth defect, loss, or other adverse outcomes. In the U.S. general population, the estimated background risk of major birth defects and miscarriage in clinically recognized pregnancies is 2% to 4% and 15% to 20%, respectively.

Data
Human Data

While available studies cannot definitively establish the absence of risk, published data from case-control studies and case reports over several decades have not identified an association with cephalosporin use during pregnancy and major birth defects, miscarriage, or other adverse maternal or fetal outcomes. Available studies have methodologic limitations, including small sample size, retrospective data collection, and inconsistent comparator groups.

Animal Data

Reproduction studies have been performed in rats, mice and rabbits administered cefazolin during organogenesis at doses of 2000, 4000 and 240 mg/kg/day (approximately 1 to 3 times the maximum recommended human dose on a body surface area comparison). There was no evidence of any adverse effects on embryofetal development due to cefazolin. In a peri‑postnatal study in rats, cefazolin administered subcutaneously up to 1200 mg/kg/day (approximately 2 times the MRHD based on body surface area comparison) to pregnant dams prior to delivery and through lactation caused no adverse effects on offspring.

8.2 Lactation

Risk Summary
Data from published literature report that cefazolin is present in human milk, but is not expected to accumulate in a breastfed infant. There are no data on the effects of cefazolin on the breastfed child or on milk production.

The developmental and health benefits of breastfeeding should be considered along with the mother’s clinical need for Cefazolin in Dextrose Injection and any potential adverse effects on the breastfed child from Cefazolin in Dextrose Injection or from the mother’s underlying condition.

8.4 Pediatric Use

Cefazolin in Dextrose Injection is indicated for the treatment of respiratory tract infections, urinary tract infections, skin and skin structure infections, biliary tract infections, bone and joint infections, genital infections, septicemia, and endocarditis in pediatric patients for whom appropriate dosing with this formulation can be achieved and for perioperative prophylaxis in pediatric patients aged 10 to 17 years old [see Indications and Usage (1.1 to 1.8)].

Safety and effectiveness of Cefazolin in Dextrose Injection in premature infants and neonates have not been established and is not recommended for use in this age group of pediatric patients. Dosing for cefazolin in pediatric patients younger than one month old has not been established.

Because of the limitations of the available strengths and administration requirements (i.e., administration of fractional doses is not recommended) of Cefazolin in Dextrose Injection, and to avoid unintentional overdose, this product is not recommended for use if a dose of Cefazolin in Dextrose Injection that does not equal 1 gram or 2 grams is required and an alternative formulation of cefazolin should be considered [see Dosage and Administration (2.2, 2,3, 2.4 and 2.5)].

The safety and effectiveness of cefazolin for injection and dextrose injection for perioperative prophylaxis have been established in pediatric patients aged 10 to 17 years old. Use of cefazolin for injection and dextrose injection in these age groups is supported by evidence from adults with additional safety and pharmacokinetic data in pediatric patients aged 10 to 17 years old. Safety and pharmacokinetics were evaluated in two multicenter, non-comparative studies (Study 1 and Study 2). These studies were conducted to assess the safety and pharmacokinetics of a single 30-minute infusion of either 1 gram or 2 grams (based on weight) of cefazolin for injection and dextrose injection for perioperative prophylaxis in pediatric patients. Study 1 evaluated the safety and pharmacokinetics of 1 g of cefazolin for injection and dextrose injection in pediatric patients aged 10 to 17 years old scheduled for surgery with a weight of at least 25 kg but less than 60 kg and 2 g in pediatric patients with a weight of at least 60 kg. Study 2 evaluated 1 g of another cefazolin injection product in pediatric patients aged 10 to 12 years old scheduled for surgery with a weight of at least 25 kg but less than 50 kg and 2 g in pediatric patients with a weight of at least 50 kg to less than 85 kg [see Dosage and Administration (2.3), Adverse Reactions (6.1) and Clinical Pharmacology (12.3)].

The safety and effectiveness of Cefazolin in Dextrose Injection for perioperative prophylaxis have not been established in pediatric patients younger than 10 years old.

8.5 Geriatric Use

Of the 920 subjects who received cefazolin in clinical studies, 313 (34%) were 65 years and over, while 138 (15%) were 75 years and over. No overall differences in safety or effectiveness were observed between these subjects and younger subjects. Other reported clinical experience has not identified differences in responses between the elderly and younger patients, but greater sensitivity of some older individuals cannot be ruled out.

This drug is known to be substantially excreted by the kidney, and the risk of toxic reactions to this drug may be greater in patients with impaired renal function. Because elderly patients are more likely to have decreased renal function, care should be taken in dose selection, and it may be useful to monitor renal function [see Dosage and Administration (2.3) and Warnings and Precautions (5.2)].

8.6 Patients with Renal Impairment

When Cefazolin in Dextrose Injection is administered to adult and pediatric patients with low urinary output because of impaired renal function (creatinine clearance less than 55 mL/min and 70 mL/min for adults and pediatric patients, respectively), lower daily dosage is required [see Dosage and Administration (2.4) and Warnings and Precautions (5.2)].

10 OVERDOSAGE

Accidental overdosage resulting in seizures may occur in patients with renal impairment who receive doses greater than the recommended dosage of Cefazolin in Dextrose Injection [see Warnings and Precautions (5.2)]. If seizures associated with accidental overdosage occur, discontinue Cefazolin in Dextrose Injection and give supportive treatment.

11 DESCRIPTION

Cefazolin in Dextrose Injection is a frozen, premixed, iso-osmotic, sterile, nonpyrogenic, single-dose solution containing either 1 g Cefazolin, USP, equivalent to 1.05 g Cefazolin Sodium, USP per 50 mL, 2 g Cefazolin, USP, equivalent to 2.1 g Cefazolin Sodium, USP per 100 mL or 3 g Cefazolin, USP, equivalent to 3.15 g Cefazolin Sodium, USP per 150 mL Galaxy container (PL 2040 Plastic). Dextrose, USP has been added to adjust osmolality (4 % as dextrose hydrous). The approximate osmolality for Cefazolin in Dextrose Injection is 290 mOsmol/kg.

Cefazolin Sodium is a semi-synthetic cephalosporin antibacterial for parenteral administration and has the following IUPAC nomenclature: Sodium (6R,7R)-3-[[(5-methyl-1,3,4- thiadiazol-2-yl)thio]methyl]-8-oxo-7-[2-(1H-tetrazol-1-yl)acetamido]-5-thia-1-azabicyclo[4.2.0]oct-2- ene-2-carboxylate. Its molecular formula is C14H13N8O4S3·Na and its molecular weight is 454.51 (free acid).

Cefazolin Sodium USP has the following structural formula:

The sodium content is 48 mg/g of cefazolin sodium.

The pH of Cefazolin in Dextrose Injection may have been adjusted with sodium bicarbonate, or sodium hydroxide/hydrochloric acid during manufacture. Water for injection, USP is added as drug vehicle. Contains no preservative. The solution is intended for intravenous use after thawing to room temperature.

This Galaxy container (PL 2040 Plastic) is fabricated from a specially designed multilayer plastic (PL 2040). Solutions are in contact with the polyethylene layer of this container and can leach out certain chemical components of the plastic in very small amounts within the expiration period. However, the suitability of the plastic has been confirmed in tests in animals according to the USP biological tests for plastic containers, as well as by tissue culture toxicity studies.

12 CLINICAL PHARMACOLOGY

12.1 Mechanism of Action

Cefazolin is an antibacterial drug [see Microbiology (12.4)].

12.2 Pharmacodynamics

The pharmacokinetic/pharmacodynamic relationship for cefazolin has not been evaluated in patients.

12.3 Pharmacokinetics

Studies have shown that following intravenous administration of cefazolin to normal subjects, mean serum concentrations peaked at approximately 185 mcg/mL and were approximately 4 mcg/mL at 8 hours for a 1 gram dose.

The serum half-life for cefazolin is approximately 1.8 hours following IV administration.

In a study of constant intravenous infusion with dosages of 3.5 mg/kg for 1 hour (approximately 250 mg) and 1.5 mg/kg the next 2 hours (approximately 100 mg), cefazolin serum concentrations at the third hour of approximately 28 mcg/mL.

Plasma pharmacokinetic parameters of cefazolin in healthy adult subjects (N=12) following a single 15- minute IV infusion of 2 grams of cefazolin for injection and dextrose injection are summarized in Table 7.

Table 7: Mean (Standard Deviation) Plasma Pharmacokinetic Parameters of Cefazolin in Healthy Adult Subjects
 | N | Cmax (mcg/mL) | Tmax [Tmax reported as median (range)] (h) | AUC0-inf (mcg*h/mL) | T1/2 (h) | CL (L/h) | Vz (L)
Single 2 grams Dose as a 15- Minute IV Infusion | 12 | 280.9 (45.9) | 0.25 (0.25-0.33) | 509.9 (89.3) | 2.01 (0.28) | 4.03 (0.68) | 11.50 (1.53)

N= number of subjects observed; Cmax = maximum plasma concentration; Tmax = time to maximum plasma concentration; AUC0-inf = area under the plasma concentration-time curve extrapolated to infinity; t1/2 = apparent plasma terminal elimination half-life; CL = total clearance; Vz = volume of distribution

Plasma pharmacokinetic parameters of cefazolin in healthy adult subjects with a weight of greater than or equal to 120 kg (N=12) following a single 30-minute IV infusion of 3 grams of Cefazolin in Dextrose Injection are summarized in Table 8.

Table 8: Mean (Standard Deviation) Plasma Pharmacokinetic Parameters of Cefazolin in Healthy Adult Subjects ≥ 120 kg
 | N | Cmax (mcg/mL) | Tmax [Tmax reported as median (range)] (h) | AUC0-inf (mcg*h/mL) | T1/2 (h) | CL (L/h) | Vz (L)
Single 3 grams Dose as a 30-Minute IV Infusion | 12 | 223 (26.0) | 0.55 (0.54-1.26) | 585 (76.5) | 2.29 (0.28) | 5.20 (0.67) | 17.0 (1.54)

N= number of subjects observed; Cmax = maximum plasma concentration; Tmax = time to maximum plasma concentration; AUC0-inf = area under the plasma concentration-time curve extrapolated to infinity; t1/2 = apparent plasma terminal elimination half-life; CL = total clearance; Vz = volume of distribution

Studies in patients hospitalized with infections indicate that cefazolin produces mean peak serum concentrations approximately equivalent to those seen in healthy subjects.

Bile concentrations in patients without obstructive biliary disease can reach or exceed serum concentrations by up to five times; however, in patients with obstructive biliary disease, bile concentrations of cefazolin are considerably lower than serum concentrations (less than 1.0 mcg/mL).

In synovial fluid, the cefazolin concentration becomes comparable to that reached in serum at about 4 hours after drug administration.

Studies of cord blood show prompt transfer of cefazolin across the placenta. Cefazolin is present in very low concentrations in the milk of nursing mothers.

Cefazolin is excreted unchanged in the urine. In the first 6 hours approximately 60% of the drug is excreted in the urine and this increases to 70% to 80% within 24 hours.

Specific Populations

Pediatric Patients for Perioperative Prophylaxis

A simulation based on pharmacokinetic data from healthy adults (n=24), pediatric patients aged 10 to 17 years (n=26: Study 1 [see Adverse Reactions (6.1)]), and pediatric patients aged 10 to 12 years (n=12: Study 2 [see Adverse Reactions (6.1)] indicate that the administration of a 1 gram dose of cefazolin for injection and dextrose injection for pediatric patients weighing less than 50 kg and a 2 grams dose of cefazolin for injection and dextrose injection for those weighing 50 kg or greater will provide comparable exposures between pediatric patients aged 10 to 17 years and healthy adults receiving 2 grams Cefazolin in Dextrose Injection [see Dosage and Administration (2.2 and 2.3) and Use in Specific Populations (8.4)].

12.4 Microbiology

Mechanism of Action

Cefazolin is a bactericidal agent that acts by inhibition of bacterial cell wall synthesis.

Resistance

Predominant mechanisms of bacterial resistance to cephalosporins include the presence of extended- spectrum beta-lactamases and enzymatic hydrolysis.

Antimicrobial Activity

Cefazolin has been shown to be active against most isolates of the following microorganisms, both in vitro and in clinical infections [see Indications and Usage (1)].

Gram-Positive Bacteria
Staphylococcus aureus
Staphylococcus epidermidis
Streptococcus agalactiae
Streptococcus pneumoniae
Streptococcus pyogenes

Methicillin-resistant staphylococci are uniformly resistant to cefazolin.

Gram-Negative Bacteria
Escherichia coli
Proteus mirabilis

Most isolates of indole positive Proteus (Proteus vulgaris), Enterobacter spp., Morganella morganii, Providencia rettgeri, Serratia spp., and Pseudomonas spp. are resistant to cefazolin.

Susceptibility Testing

For specific information regarding susceptibility test interpretive criteria, and associated test methods and quality control standards recognized by FDA for this drug, please see: http://www.fda.gov/STIC.

13 NONCLINICAL TOXICOLOGY

13.1 Carcinogenesis, Mutagenesis, Impairment of Fertility

Carcinogenicity and Mutagenesis

Mutagenicity studies and long-term studies in animals to determine the carcinogenic potential of Cefazolin in Dextrose Injection have not been performed.

Impairment of Fertility

Fertility studies conducted in rats subcutaneously administered cefazolin at doses of

2000 mg/kg/day (approximately 3 times the maximum recommended human dose based on body surface area comparison) showed no impairment of mating and fertility.

15 REFERENCES

1. Czarny D, Prichard PJ, Fennessy M, Lewis S. Anaphylactoid reaction to 50% solution of dextrose. Med J Aust 1980;2:255-258.
2. Guharoy, SR, Barajas M. Probably Anaphylactic Reaction to Corn-Derived Dextrose Solution. Vet Hum Toxicol 1991;33:609-610.

16 HOW SUPPLIED/STORAGE AND HANDLING

Cefazolin in Dextrose Injection is supplied as a premixed, frozen, iso-osmotic, sterile, nonpyrogenic solution in single-dose Galaxy plastic containers as follows:

Product Description | Number of Containers/Carton | NDC Number
1 gram cefazolin in 50 mL (20 mg/mL) | 24 count | NDC 0338-3503-41
2 grams cefazolin in 100 mL (20 mg/mL) | 12 count | NDC 0338-3508-41
3 grams cefazolin in 150 mL (20 mg/mL) | 6 count | NDC 0338-0096-06

Store in a freezer capable of maintaining a temperature of -20°C (-4°F) or below.

Handle frozen product containers with care. Product containers may be fragile in the frozen state.

Thaw frozen container at room temperature 20°C to 25°C (68°F to 77°F) or under refrigeration 2°C to 8°C (36°F to 46°F). Do not force thaw by immersion in water baths or by microwave irradiation.

The thawed solution is stable for 30 days under refrigeration (5°C/41°F) or 48 hours at 25°C/77°F. Do not refreeze [see Dosage and Administration (2.5)].

17 PATIENT COUNSELING INFORMATION

Serious Allergic Reactions

Advise patients that allergic reactions, including serious allergic reactions could occur and that serious reactions require immediate treatment and discontinuation of Cefazolin in Dextrose Injection. Patients should report to their health care provider any previous allergic reactions to cefazolin, cephalosporins, penicillins, or other similar antibacterials.

Seizures

Advise patients that seizures could occur with Cefazolin in Dextrose Injection. Instruct patients to inform a healthcare provider at once of any signs and symptoms of seizures, for immediate treatment, dosage adjustment, or discontinuation of Cefazolin in Dextrose Injection.

Diarrhea

Advise patients that diarrhea is a common problem caused by antibacterials, which usually ends when the antibacterial is discontinued. Sometimes after starting treatment with antibacterials, patients can develop watery and bloody stools (with or without stomach cramps and fever) even as late as two or more months after having taken the last dose of the antibacterials. If this occurs, patients should contact a physician as soon as possible.

Antibacterial Resistance

Patients should be counseled that antibacterial drugs, including Cefazolin in Dextrose Injection should only be used to treat bacterial infections. They do not treat viral infections (e.g., the common cold). When Cefazolin in Dextrose Injection is prescribed to treat a bacterial infection, patients should be told that although it is common to feel better early in the course of therapy, the medication should be taken exactly as directed. Skipping doses or not completing the full course of therapy may (1) decrease the effectiveness of the immediate treatment and (2) increase the likelihood that bacteria will develop resistance and will not be treatable by Cefazolin in Dextrose Injection or other antibacterial drugs in the future.

Baxter
Baxter Healthcare Corporation
Deerfield, IL 60015

Made in USA

07-19-05-387

Baxter and Galaxy are trademarks of Baxter International Inc. or its subsidiaries.

Any other trademarks, product brands or images appearing herein are the property of their respective owners.

PACKAGE/LABEL PRINCIPAL DISPLAY PANEL

Container Label

Cefazolin in Dextrose
Injection, USP
1 g / 50 mL
(20 mg / mL)

GALAXY
Single Dose Container
Discard unused portion

NDC 0338-3503-41
Code 2G3503
Sterile Nonpyrogenic
Iso-osmotic

Each 50 mL contains: 1 g Cefazolin, USP, equivalent to 1.05 g Cefazolin
Sodium, USP with approx. 2 g Dextrose Hydrous, USP added to adjust
osmolality, and Water for Injection, USP. pH may have been adjusted with
sodium bicarbonate or sodium hydroxide/hydrochloric acid.

Dosage: For Intravenous Infusion Only. See prescribing information.
Cautions: Do not add supplementary medication or additives.

Rx only

Store at or below -20°C (-4°F). Thaw at room temperature 20°C to 25°C (68°F to
77°F) or under refrigeration 2°C to 8°C (36°F to 46°F). DO NOT FORCE
THAW BY IMMERSION IN WATER BATHS OR BY MICROWAVE IRRADIATION.
Thawed solution is stable for 30 days under refrigeration or 48 hours at room
temperature. Do not refreeze.

Baxter Logo

Baxter and Galaxy are registered trademarks of
Baxter International Inc.
Manufactured by Baxter Healthcare Corporation
Deerfield, IL 60015 USA
Made in US

PL2040 Plastic

07-34-00-1642

* BAR CODE POSITION
ONLY

303383503411

Carton Label

Thaw at room temperature 20°C to 25°C (68°F to 77°F) or under refrigeration 2°C to 8°C (36°F to 41°F).
DO NOT FORCE THAW BY IMMERSION IN WATER BATHS OR BY MICROWAVE IRRADIATION. Thawed solution is stable for 30 days under refrigeration or 48 hours at room temperature.
Do not refreeze.
Handle frozen product containers with care. Product containers may be fragile in the
frozen state.
Baxter and Galaxy are registered trademarks of Baxter International Inc.
PL 2040 Plastic

07-04-00-0801

Cefazolin in Dextrose Injection, USP
1 g / 50 mL (20 mg / mL)
Contains 12 units of Single Dose bags. Each bag contains 50 mL Iso-osmotic
Store at or below -20°C (-4°F). Do not refreeze.

Rx Only

NDC 0338-3503-41
Code 2G3503

*FOR BAR CODE POSITION ONLY
(01) 20303383503415

GALAXY Container
Sterile Nonpyrogenic
Each 50 mL contains: 1g Cefazolin, USP, equivalent to 1.05 g Cefazolin Sodium, USP with approx. 2 g
Dextrose Hydrous, USP added to adjust osmolality, and Water for Injection, USP. pH may have been adjusted
with sodium bicarbonate or sodium hydroxide/hydrochloric acid.

Dosage: For Intravenous Infusion Only. See prescribing information.

Cautions: Do not add supplementary medications or additives.

Baxter Logo

Baxter and Galaxy are registered trademarks of Baxter International, Inc.
Baxter Healthcare Corporation Deerfield, IL 60015 USA

Container Label

Cefazolin in Dextrose
Injection, USP
2 g / 100 mL
(20 mg / mL)

GALAXY
Single Dose Container
Discard unused portion

NDC 0338-3508-41
Code 2G3508
Sterile Nonpyrogenic
Iso-osmotic

Each 100 mL contains: 2 g Cefazolin, USP, equivalent to 2.1 g Cefazolin
Sodium, USP with approx. 4 g Dextrose Hydrous, USP added to adjust
osmolality, and Water for Injection, USP. pH may have been adjusted with
sodium bicarbonate or sodium hydroxide/hydrochloric acid.

Dosage: For Intravenous Infusion Only. See prescribing information.
Cautions: Do not add supplementary medication or additives.

Rx only

Store at or below -20°C (-4°F). Thaw at room temperature 20°C to 25°C (68°F to
77°F) or under refrigeration 2°C to 8°C (36°F to 46°F). DO NOT FORCE THAW
BY IMMERSION IN WATER BATHS OR BY MICROWAVE IRRADIATION. Thawed
solution is stable for 30 days under refrigeration or 48 hours at room
temperature. Do not refreeze.

Baxter Logo

Baxter and Galaxy are registered trademarks of Baxter International Inc.
Manufactured by Baxter Healthcare Corporation Deerfield, IL 60015 USA
Made in USA

PL2040 Plastic

07-34-00-1643

BAR CODE POSITION
ONLY

303383508416

Carton Label

Thaw at room temperature 20°C to 25°C (68°F to 77°F) or under refrigeration 2°C to 8°C (36 °F to 41°F).
DO NOT FORCE THAW BY IMMERSION IN WATER BATHS OR BY MICROWAVE IRRADIATION. Thawed solution is stable for 30 days under refrigeration or 48 hours at room temperature.
Do not refreeze.
Handle frozen product containers with care. Product containers may be fragile in the
frozen state.
PL 2040 Plastic
07-04-00-0802

Cefazolin in Dextrose Injection, USP
2 g / 100 mL (20 mg/ mL)
Contains 6 units of Single Dose bags. Each bag contains 100 mL. Iso-osmotic
Store at or below -20°C (4°F). Do not refreeze.
Lot XXXXXX Exp. DD MMM YY

Rx Only

NDC 0338-3508-41
Code 2G3508

*FOR BAR CODE POSITION ONLY
(01) 20303383508410

GALAXY Container
Sterile Nonpyrogenic
Each 100 mL contains: 2 g Cefazolin, USP, equivalent to 2.1 g Cefazolin Sodium, USP with approx. 4 g
Dextrose Hydrous, USP added to adjust osmolality, and Water for Injection, USP. pH may have been
adjusted with sodium bicarbonate or sodium hydroxide/hydrochloric acid.

Dosage: For Intravenous Infusion Only. See prescribing information.
Cautions: Do not add supplementary medications or additives.

Baxter Logo

Baxter and Galaxy are registered trademarks of Baxter International, Inc.
Baxter Healthcare Corporation Deerfield, IL 60015 USA

Container Label

Cefazolin
in Dextrose Injection, USP
3 g / 150 mL (20 mg / mL)

3 g

GALAXY
Single Dose Container
Discard unused portion

NDC 0338-0096-06
Code 2G3509
Sterile Nonpyrogenic
Iso-osmotic

Each 150 mL contains: 3 g Cefazolin, USP, equivalent to
3.15 g Cefazolin Sodium, USP with approx. 6 g Dextrose
Hydrous, USP added to adjust osmolality, and Water for
Injection, USP. pH may have been adjusted with sodium
hydroxide or hydrochloric acid.

Dosage: For Intravenous Infusion Only. See prescribing
information.

Caution: Do not add supplementary medication or additives.

Rx only

Store at or below -20°C (-4°F). Thaw at room temperature
20°C to 25°C (68°F to 77°F) or under refrigeration 2°C to 8°C
(36°F to 46°F). DO NOT FORCE THAW BY IMMERSION
IN WATER BATHS OR BY MICROWAVE IRRADIATION.
Thawed solution is stable for 30 days under refrigeration
or 48 hours at room temperature. Do not refreeze.

Baxter Logo

Manufactured by Baxter Healthcare Corporation,
Deerfield, IL 60015 USA

PL2040 Plastic

07-34-00-1721

BAR CODE
POSITION ONLY UPC-A

303380096060

Carton Label

Thaw at room temperature 20°C to 25°C (68°F to 77°F) or under refrigeration 2°C to 8°C (36 °F to 41°F).
DO NOT FORCE THAW BY IMMERSION IN WATER BATHS OR BY MICROWAVE IRRADIATION. Thawed solution is stable for 30 days under refrigeration or 48 hours at room temperature.
Do not refreeze.
Handle frozen product containers with care. Product containers may be fragile in the frozen state.

PL 2040 Plastic

07-04-00-0843

Cefazolin
in Dextrose Injection, USP
3 g / 150 mL (20 mg / mL)

3 g

Rx Only

Contains 3 units of Single-Dose bags.
Each bag contains 150 mL.
Store at or below -20°C (-4°F). Do not refreeze.

NDC 0338-0096-06
Code 2G3509

*FOR BAR CODE POSITION ONLY
(01) 20303380096064

GALAXY Container
Sterile Nonpyrogenic
Each 150 mL contains: 3 g Cefazolin, USP, equivalent to 3.15 g Cefazolin Sodium, USP with approx. 6 g Dextrose Hydrous, USP added to adjust osmolality, and Water for Injection, USP. pH may have been adjusted with sodium hydroxide or hydrochloric acid.
Dosage: For Intravenous Infusion Only. See prescribing information
Caution: Do not add supplementary medications or additives.

Baxter Logo

Baxter Healthcare Corporation Deerfield, IL 60015 USA